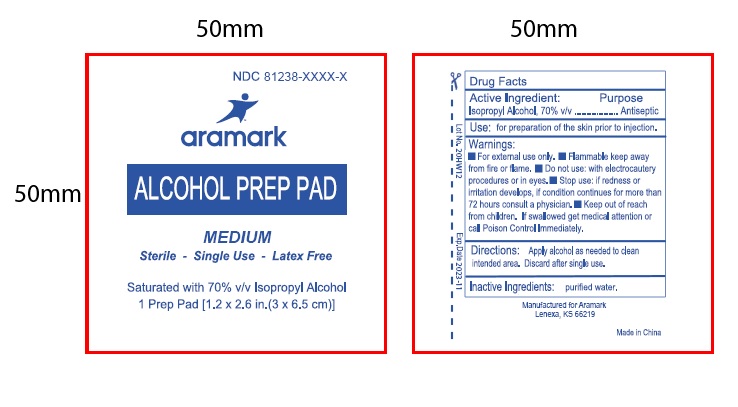 DRUG LABEL: Alcohol Prep Pad
NDC: 81238-0008 | Form: CLOTH
Manufacturer: Western First Aid Safety dba Aramark
Category: otc | Type: HUMAN OTC DRUG LABEL
Date: 20210520

ACTIVE INGREDIENTS: ISOPROPYL ALCOHOL 0.70 mL/1 mL
INACTIVE INGREDIENTS: WATER

aramark Alcohol Prep Pad

Drug Facts

Active Ingredient:

Isopropyl Alcohol 70% v/v

Purpose: Antiseptic

INDICATIONS AND USAGE

Use: for preparation of the skin prior to injection.

Warnings:

■ For external use only. ■ Flammable. Keep away

from fire or flame. ■ Do not use: with electrocautery

procedures or in eyes. ■ Stop use: if redness or

irritation develops, if condition continues for more than

72 hours consult a physician.

KEEP OUT OF REACH OF CHILDREN

■ Keep out of reach from children. If swallowed, get medical attention or

call Poison Control Immediately.

DOSAGE AND ADMINISTRATION

Directions: Apply alcohol as needed to clean intended area. Discard after single use.

Inactive Ingredients: purified water.

Product Label

NDC 81238-0008-1

aramark

ALCOHOL PREP PAD

MEDIUM

Sterile - Single Use - Latex Free

Saturated with 70% v/v Isopropyl Alcohol

1 Prep Pad [1.2 x 2.6 in. (3 x 6.5 cm)]
Manufactured for Aramark

Lenexa, KS 66219

Made in China

res